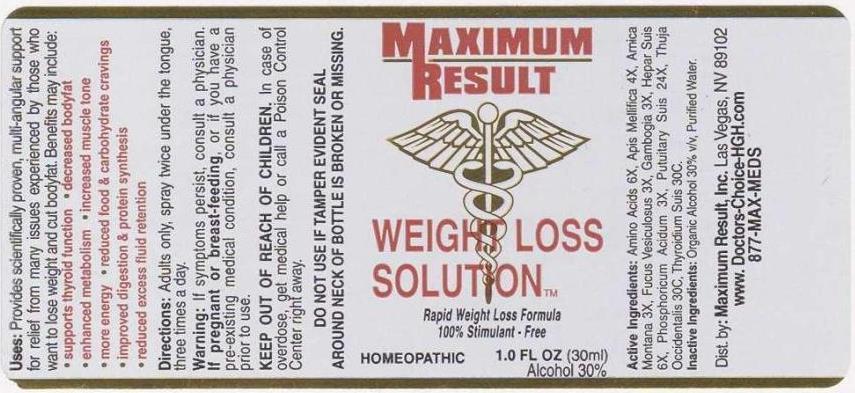 DRUG LABEL: Weight Loss Solution
NDC: 49415-0002 | Form: SPRAY
Manufacturer: Maximum  Results Solution, Inc.
Category: homeopathic | Type: HUMAN OTC DRUG LABEL
Date: 20131025

ACTIVE INGREDIENTS: AMINO ACIDS 6 [hp_X]/1 mL; APIS MELLIFERA 4 [hp_X]/1 mL; ARNICA MONTANA 3 [hp_X]/1 mL; FUCUS VESICULOSUS 3 [hp_X]/1 mL; GAMBOGE 3 [hp_X]/1 mL; PORK LIVER 6 [hp_X]/1 mL; PHOSPHORIC ACID 3 [hp_X]/1 mL; SUS SCROFA PITUITARY GLAND 24 [hp_X]/1 mL; THUJA OCCIDENTALIS LEAF 30 [hp_C]/1 mL; SUS SCROFA THYROID 30 [hp_C]/1 mL
INACTIVE INGREDIENTS: WATER; ALCOHOL

DRUG FACTS:

ACTIVE INGREDIENTS:

Amino Acids 6X, Apis Mellifica 4X, Arnica Montana 3X, Fucus Vesiculosus 3X, Gambogia 3X, Hepar Suis 6X, Phosphoricum Acidum 3X, Pituitaria Glandula Suis 24X, Thuja Occidentalis 30C, Thyroidinum Suis 30C.

USES:

Provides scientifically proven, multi-angular support for relief from many issues experienced by those who want to lose weight and cut bodyfat. Benefits may include:

- supports thyroid function - decreased bodyfat - enhanced metabolism - increased muscle tone - more energy - reduced food & carbohydrate cravings - improved digestion & protein synthesis - reduced excess fluid retention

WARNINGS:

If symptoms persist, consult a physician. If pregnant or breast-feeding, or if you have a pre-exisiting medical conditin, consult a physician prior to use.

KEEP OUT OF REACH OF CHILDREN. In case of overdose, get medical help or call a Poison Control Center right away.

DO NOT USE IF TAMPER EVIDENT SEAL AROUND NECK OF BOTTLE IS BROKEN OR MISSING.

KEEP OUT OF REACH OF CHILDREN. In case of overdose, get medical help or contact a Poison Control Center right away.

DIRECTIONS:

Adults only, spray twice under the tongue, three times a day.

INDICATIONS:

Provides scientifically proven, multi-angular support for relief from many issues experienced by those who want to lose weight and cut bodyfat. Benefits may include:

- supports thyroid function - decreased bodyfat - enhanced metabolism - increased muscle tone - more energy - reduced food & carbohydrate cravings - improved digestion & protein synthesis - reduced excess fluid retention

INACTIVE INGREDIENTS:

Organic Alcohol 30% v/v, Purified Water.

QUESTIONS:

Dist. by: Maximum Result, Inc. Las Vegas, NV 89102

www.Doctors-Choice-HGH.com

877-MAX-MEDS

PACKAGE DISPLAY LABEL:

MAXIMUM

RESULT

WEIGHT LOSS

SOLUTION

HOMEOPATHIC

1.O FL OZ (30ml)

Alcohol 30%